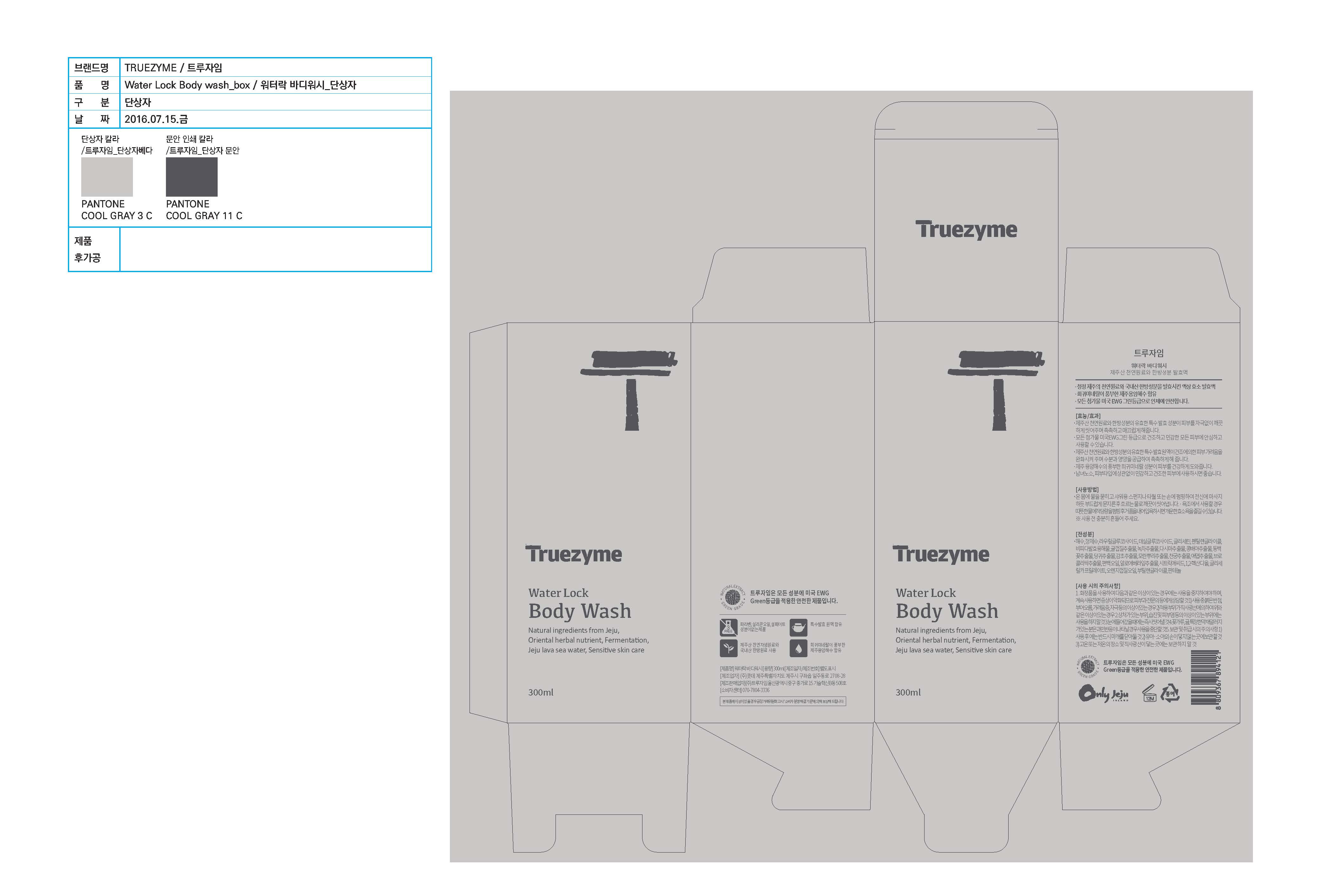 DRUG LABEL: Truezyme Water Lock Body Wash
NDC: 71076-0003 | Form: LIQUID
Manufacturer: Truezyme Co., Ltd.
Category: otc | Type: HUMAN OTC DRUG LABEL
Date: 20161116

ACTIVE INGREDIENTS: GLYCERIN 3.5 g/100 mL
INACTIVE INGREDIENTS: LAURYL GLUCOSIDE; ALOE VERA LEAF; WATER

Drug Facts

Active ingredient

Glycerin

Purpose

Cleanse, moisturize, and smoothen the skin gently.

DOSAGE AND ADMINISTRATION

For external use only

INDICATIONS AND USAGE

- Wet the whole body and lather well on a shower sponge, a towel, or hands and massage the whole body gently and wash away with water cleanly.

- For a bath, you can enjoy a refreshing enzymatic bath by lathering enough in warm water.

* Shake well before use.

Inactive ingredients:

Sea Water, Lauryl Glucoside, Aloe Barbadensis Leaf Extract, Panthenol, etc.

Keep out of reach of children.

WARNINGS

1. Stop using the product if there are any of the following abnormal symptoms appearing after use and consult with your dermatologist as continued use can worsen the symptoms.

1) If there are red spots, swelling, itchiness, or irritation

2) If the above symptoms appear around the skin to which the product has been applied after being exposed to direct sunlight.

2. Do not apply the product to any parts of the skin with wound, eczema, or dermatitis.

3. If it gets into eye, wash the eye with clean water immediately.

4. Those who are allergic to certain medicinal herb, such as pollen and tangerine, must stop using the product if they experience hypersensitivity.

5. Precautions on storage and handling

1) Make sure to close the cap after use.

2) Keep out of the reach of children.

3) Do not keep the product in a hot or cold place or a place getting direct sunlight.